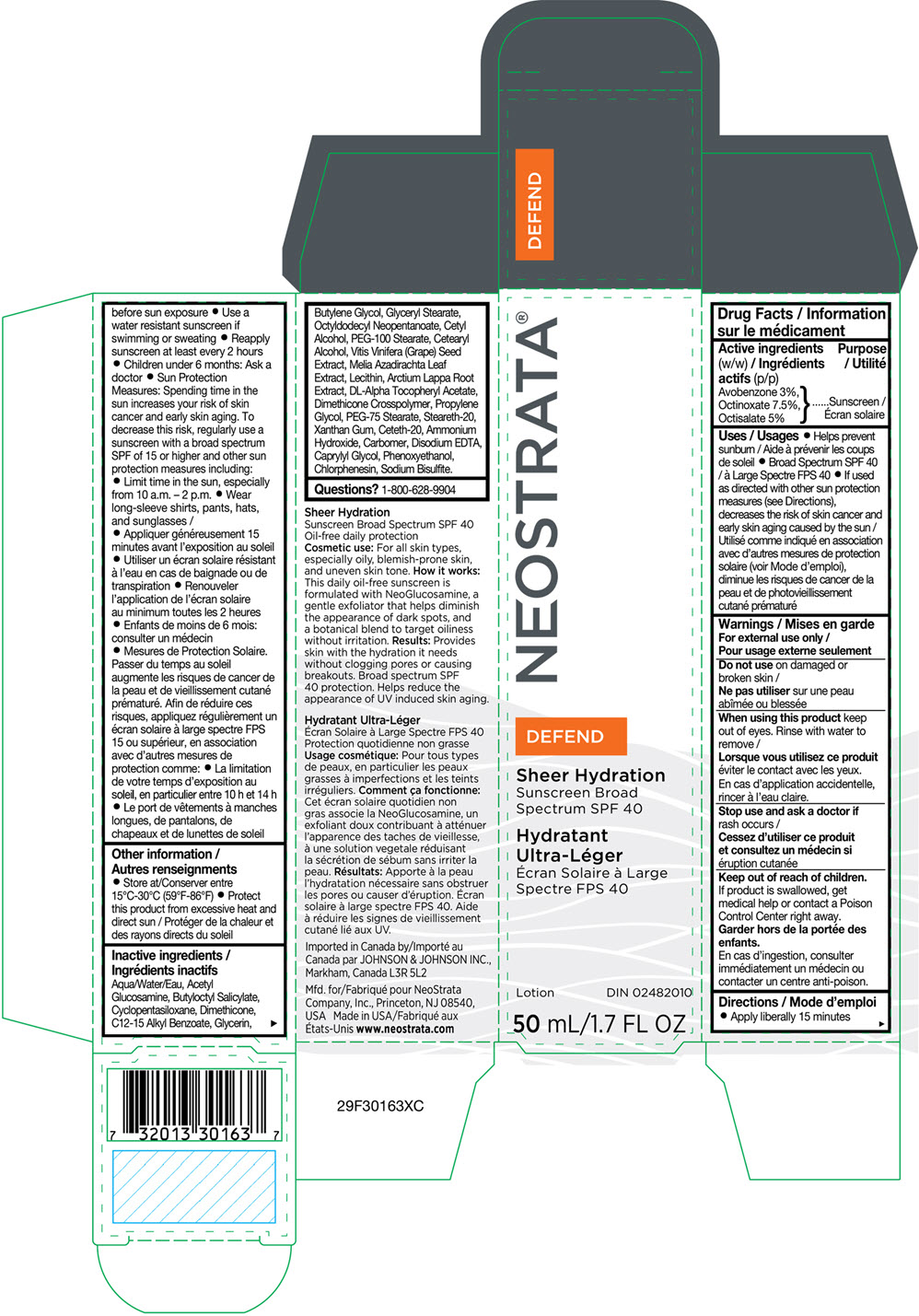 DRUG LABEL: NeoStrata Sheer Hydration
NDC: 58414-0020 | Form: LOTION
Manufacturer: NeoStrata Company Inc.
Category: otc | Type: HUMAN OTC DRUG LABEL
Date: 20250110

ACTIVE INGREDIENTS: OCTINOXATE 75 mg/1 mL; OCTISALATE 50 mg/1 mL; AVOBENZONE 30 mg/1 mL
INACTIVE INGREDIENTS: WATER; N-ACETYLGLUCOSAMINE; BUTYLOCTYL SALICYLATE; CYCLOMETHICONE 5; GLYCERIN; ALKYL (C12-15) BENZOATE; DIMETHICONE; BUTYLENE GLYCOL; GLYCERYL MONOSTEARATE; OCTYLDODECYL NEOPENTANOATE; CETYL ALCOHOL; PEG-100 STEARATE; CETOSTEARYL ALCOHOL; .ALPHA.-TOCOPHEROL ACETATE; AZADIRACHTA INDICA LEAF; LECITHIN, SOYBEAN; ARCTIUM LAPPA ROOT; VITIS VINIFERA SEED; PROPYLENE GLYCOL; PEG-75 STEARATE; XANTHAN GUM; EDETATE DISODIUM ANHYDROUS; CETETH-20; STEARETH-20; AMMONIA; PHENOXYETHANOL; CAPRYLYL GLYCOL; CHLORPHENESIN; SODIUM BISULFITE; CARBOMER HOMOPOLYMER, UNSPECIFIED TYPE; DIMETHICONE CROSSPOLYMER (450000 MPA.S AT 12% IN CYCLOPENTASILOXANE)

NeoStrata®Sheer Hydration
Sunscreen Broad Spectrum SPF 40

Drug Facts

Active ingredients (w/w)

Avobenzone 3%, Octinoxate 7.5%, Octisalate 5%

Purpose

Sunscreen

Uses

- Helps prevent sunburn
- Broad Spectrum SPF 40
- If used as directed with other sun protection measures (see Directions), decreases the risk of skin cancer and early skin aging caused by the sun

Warnings

For external use only

Do not useon damaged or broken skin.

WHEN USING

When using this productkeep out of eyes. Rinse with water to remove.

Stop use and ask a doctor ifrash occurs

Keep out of reach of children.If product is swallowed, get medical help or contact a Poison Control Center right away.

Directions

- Apply liberally 15 minutes before sun exposure
- Use a water resistant sunscreen if swimming or sweating
- Reapply sunscreen at least every 2 hours
- Children under 6 months: Ask a doctor
- Sun Protection Measures: Spending time in the sun increases your risk of skin cancer and early skin aging. To decrease this risk, regularly use a sunscreen with a Broad Spectrum SPF of 15 or higher and other sun protection measures including:
  - Limit time in the sun, especially from 10 a.m.–2 p.m.
  - Wear long-sleeve shirts, pants, hats, and sunglasses

Other information

- Store at 15°C-30°C (59°F-86°F)
- Protect this product from excessive heat and direct sun

Inactive ingredients

Water ,Acetyl Glucosamine, Butyloctyl Salicylate, Cyclopentasiloxane, Dimethicone, C12-15 Alkyl Benzoate, Glycerin, Butylene Glycol, Glyceryl Stearate, Octyldodecyl Neopentanoate, Cetyl Alcohol, PEG-100 Stearate, Cetearyl Alcohol, Vitis Vinifera (Grape) Seed Extract, Melia Azadirachta Leaf Extract, Lecithin, Arctium Lappa Root Extract, DL-Alpha Tocopheryl Acetate, Dimethicone Crosspolymer, Propylene Glycol, PEG-75 Stearate, Steareth-20, Xanthan Gum, Ceteth-20, Ammonium Hydroxide, Carbomer, Disodium EDTA, Caprylyl Glycol, Phenoxyethanol, Chlorphenesin, Sodium Bisulfite.

Questions?

1-800-628-9904

PRINCIPAL DISPLAY PANEL - 50 mL Bottle Carton

NEOSTRATA®

DEFEND

Sheer Hydration
Sunscreen Broad
Spectrum SPF 40

Lotion
DIN 02482010

50 mL/1.7 FL OZ